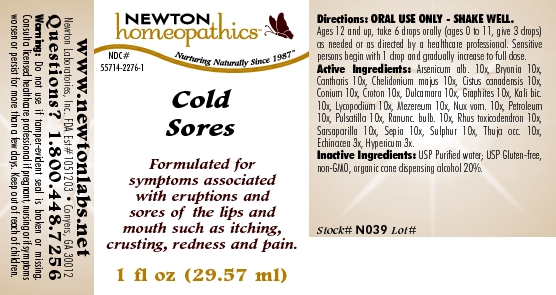 DRUG LABEL: Cold Sores 
NDC: 55714-2276 | Form: LIQUID
Manufacturer: Newton Laboratories, Inc.
Category: homeopathic | Type: HUMAN OTC DRUG LABEL
Date: 20110301

ACTIVE INGREDIENTS: Arsenic Trioxide 10 [hp_X]/1 mL; Bryonia Alba Root 10 [hp_X]/1 mL; Lytta Vesicatoria 10 [hp_X]/1 mL; Chelidonium Majus 10 [hp_X]/1 mL; Helianthemum Canadense 10 [hp_X]/1 mL; Conium Maculatum Flowering Top 10 [hp_X]/1 mL; Croton Tiglium Seed 10 [hp_X]/1 mL; Solanum Dulcamara Top 10 [hp_X]/1 mL; Graphite 10 [hp_X]/1 mL; Potassium Dichromate 10 [hp_X]/1 mL; Lycopodium Clavatum Spore 10 [hp_X]/1 mL; Daphne Mezereum Bark 10 [hp_X]/1 mL; Strychnos Nux-vomica Seed 10 [hp_X]/1 mL; Kerosene 10 [hp_X]/1 mL; Pulsatilla Vulgaris 10 [hp_X]/1 mL; Ranunculus Bulbosus 10 [hp_X]/1 mL; Toxicodendron Pubescens Leaf 10 [hp_X]/1 mL; Smilax Regelii Root 10 [hp_X]/1 mL; Sepia Officinalis Juice 10 [hp_X]/1 mL; Sulfur 10 [hp_X]/1 mL; Thuja Occidentalis Leafy Twig 10 [hp_X]/1 mL; Echinacea, Unspecified 3 [hp_X]/1 mL; Hypericum Perforatum 3 [hp_X]/1 mL
INACTIVE INGREDIENTS: Alcohol

Cold Sores

INDICATIONS & USAGE SECTION

Cold Sores Formulated for symptoms associated with eruptions and sores of the lips and mouth such as itching, crusting, redness and pain.

DOSAGE & ADMINISTRATION SECTION

Directions: ORAL USE ONLY - SHAKE WELL. Ages 12 and up, take 6 drops orally (ages 0 to 11, give 3 drops) as needed or as directed by a healthcare professional. Sensitive persons begin with 1 drop and gradually increase to full dose.

OTC - ACTIVE INGREDIENT SECTION

Arsenicum alb. 10x, Bryonia 10x, Cantharis 10x, Chelidonium majus 10x, Cistus canadensis 10x, Conium 10x, Croton 10x, Dulcamara 10x, Graphites 10x, Kali bic.10x, Lycopodium 10x, Mezereum 10x, Nux vom. 10x, Petroleum 10x, Pulsatilla 10x, Ranunc. bulb. 10x, Rhus toxicodendron 10x, Sarsaparilla 10x, Sepia 10x, Sulphur 10x, Thuja occ. 10x, Echinacea 3x, Hypericum 3x.

OTC - PURPOSE SECTION

Formulated for symptoms associated with eruptions and sores of the lips and mouth such as itching, crusting, redness and pain.

INACTIVE INGREDIENT SECTION

Inactive Ingredients: USP Purified Water; USP Gluten-free, non-GMO, organic cane dispensing alcohol 20%.

QUESTIONS SECTION

www.newtonlabs.net Newton Laboratories, Inc. FDA Est # 1051203 - Conyers, GA30012
Questions? 1.800.448.7256

WARNINGS SECTION

Warning: Do not use if tamper - evident seal is broken or missing. Consult a licensed healthcare professional if pregnant, nursing or if symptoms worsen or persist for more than a few days. Keep out of reach of children.

OTC - PREGNANCY OR BREAST FEEDING SECTION

Consult a licensed healthcare professional if pregnant, nursing or if symptoms worsen or persist for more than a few days.

OTC - KEEP OUT OF REACH OF CHILDREN SECTION

Keep out of reach of children.